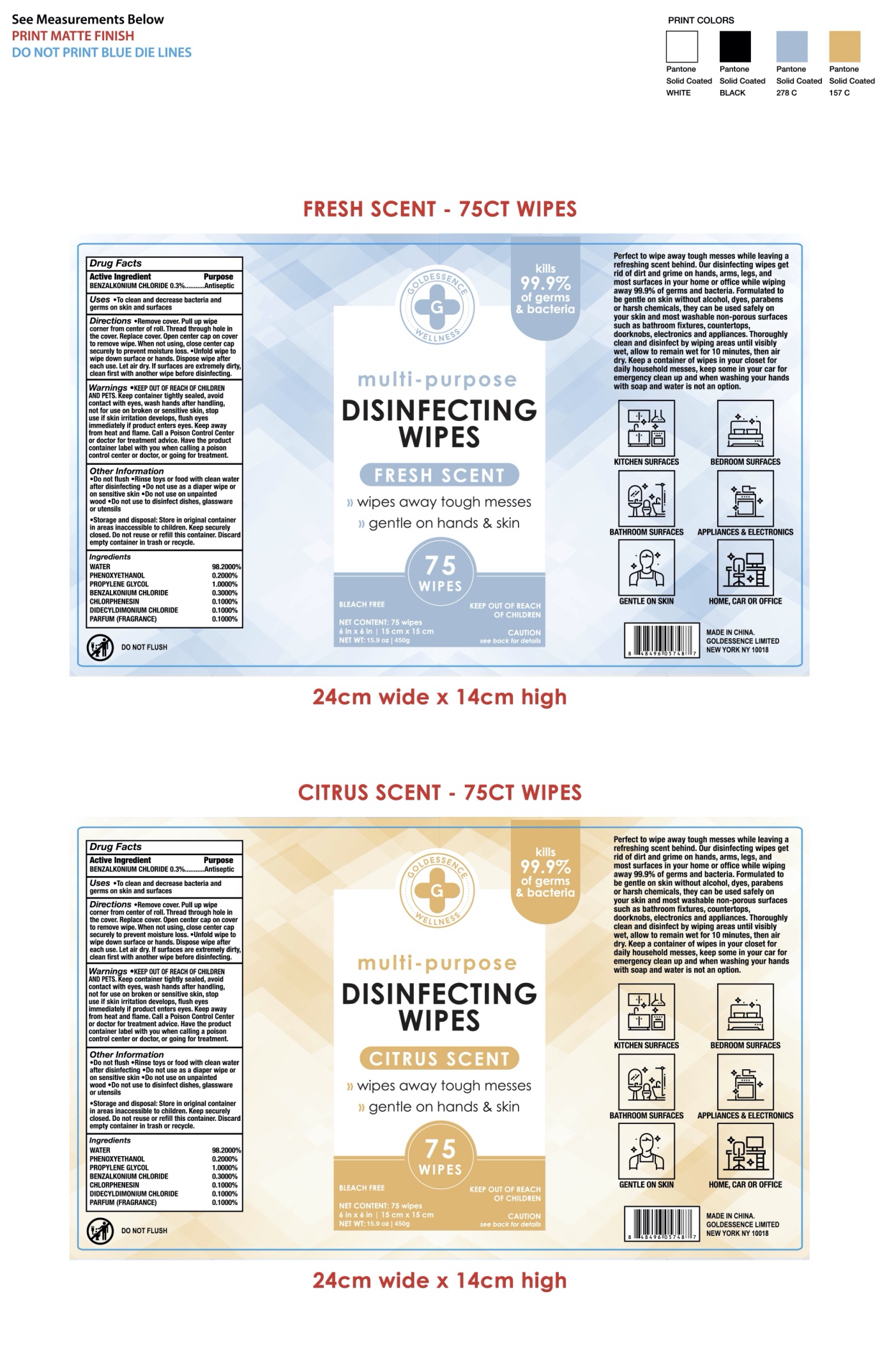 DRUG LABEL: GOLDESSENCE DISINFECTING WIPES
NDC: 76635-002 | Form: CLOTH
Manufacturer: Hangzhou Glamcos Biotech CO.,LTD
Category: otc | Type: HUMAN OTC DRUG LABEL
Date: 20231123

ACTIVE INGREDIENTS: BENZALKONIUM CHLORIDE 0.3 g/100 g
INACTIVE INGREDIENTS: CHLORPHENESIN; DIDECYLDIMONIUM CHLORIDE; FRAGRANCE LAVENDER & CHIA F-153480; PHENOXYETHANOL; PROPYLENE GLYCOL; WATER

Active Ingredient(s)

Benzalkonium Chloride 0.3%

Purpose

Antiseptic

Use

To clean and decrease bacteria and germs on skin and surfaces.

Warnings

Keep container tightly sealed,avoid contact with eyes ,wash hands after handing,not for use on broken or sensitive skin,stop use if skin irritation develops,flush eyes immediately if product enters eyes.Keep away from heat and flame.Call a poison control center or doctor for treatment advice.Have the product container label with you when calling a poison control center or doctor,or going for treatment.

Keep out of reach of children and pets.

Directions

Remove cover.Pull up wipe corner from center of roll.Thread through hole in the cover.Replace cover. Open center cap on cover to remove wipe. When not using,close center cap securely to prevent moisture loss.
Unfold wipe to wipe down surface or hands.Dispose wipe after each use.Let air dry.If surfaces are extremely dirty,clean first with another wipe before disinfecting.

Other information

Do not flush.
Rinse toys or food with clean water after disinfecting.
Do not use as a diaper wipe or on sensitive skin.
Do not use on unpainted wood.
Do not use to disinfect dishes,glassware or utensils.
Storage and disposal: Store in original container in areas inaccessible to children.Keep securely closed.Do not reuse or refill this container.Discard empty container in trash or recycle.

Perfect to wipe away tough messes while leaving a refreshing scent behind. Our disinfecting wipes get rid of dirt and grime on hand,arms,legs,and most surfaces in your home or office while wiping away 99.9% of germs and bacteria. Formulated to be gentle on skin without alcohol,dyes,parabens or harsh chemicals,they can be used safely on your skin and most washable non-porous surfaces such as bathroom fixtures,countertops,doorknobs,electronics and appliances. Thoroughly clean and disinfect by wiping areas until visibly wet,allow to remain wet for 10 minutes,then air dry. Keep a container of wipes in your closet for daily household messes,keep some in your car for emergency clean up and when washning your hands with soap and water is not an option.

Inactive ingredients

Water，Phenoxyethanol ，Propylene Glycol， Chlorphenesin，Didecyldimonium Chloride，Parfum(Fragrance)